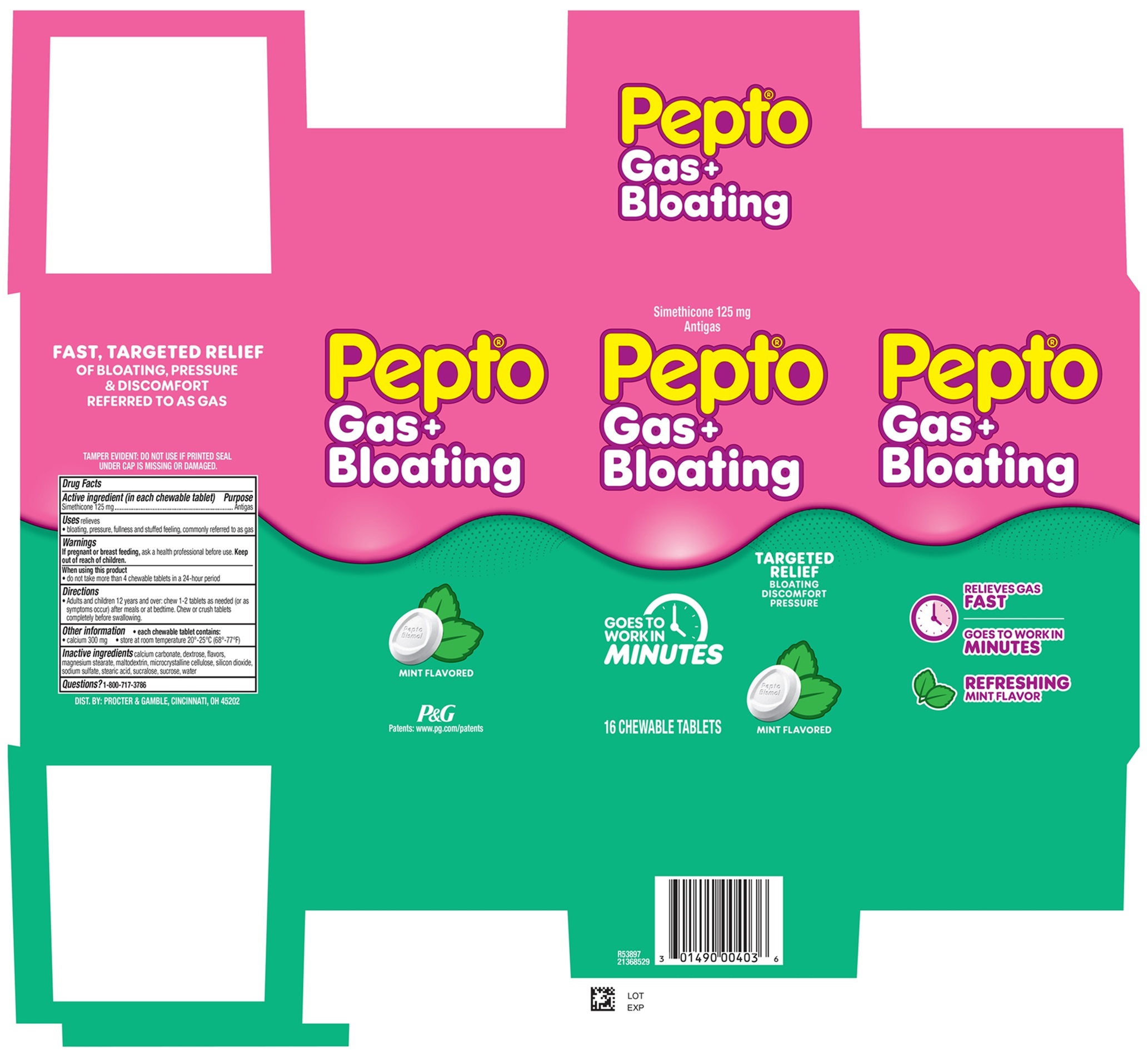 DRUG LABEL: Pepto
NDC: 84126-378 | Form: TABLET, CHEWABLE
Manufacturer: The Procter & Gamble Manufacturing Company
Category: otc | Type: HUMAN OTC DRUG LABEL
Date: 20260120

ACTIVE INGREDIENTS: DIMETHICONE 125 mg/1 1
INACTIVE INGREDIENTS: WATER; CALCIUM CARBONATE; DEXTROSE; MAGNESIUM STEARATE; MALTODEXTRIN; MICROCRYSTALLINE CELLULOSE; SODIUM SULFATE; STEARIC ACID; SUCRALOSE; SUCROSE; SILICON DIOXIDE

Pepto® Gas + Bloating

Drug Facts

Active ingredient (in each chewable tablet)

Simethicone 125 mg

Purpose

Antigas

Uses

relieves

- bloating, pressure, fullness and stuffed feeling, commonly referred to as gas

Warnings

If pregnant or breast feeding,

ask a health professional before use.

Keep out of reach of children.

When using this product

- do not take more than 4 chewable tablets in a 24-hour period

Directions

- adults and children 12 years and over: chew 1-2 tablets as needed (or as symptoms occur) after a meal or at bedtime. Chew or crush tablets completely before swallowing.

Other information

- each chewable tablet contains:
- calcium 300 mg
- store at room temperature 20°-25°C (68°-77ºF)

Inactive ingredients

calcium carbonate, dextrose, flavors, magnesium stearate, maltodextrin, microcrystalline cellulose, silicon dioxide, sodium sulfate, stearic acid, sucralose, sucrose, water

Questions?

1-800-717-3786

TAMPER EVIDENT: DO NOT USE IF PRINTED SEAL UNDER CAP IS MISSING OR DAMAGED.

DIST. BY PROCTER & GAMBLE,

CINCINNATI, OH 45202

PRINCIPAL DISPLAY PANEL - 16 CHEWABLE TABLETS

Simethicone 125 mg Antigas

Pepto Gas + Bloating

GOES TO WORK IN MINUTES

TARGETED RELIEF

BLOATING

DISCOMFORT

PRESSURE

MINT FLAVORED

16 CHEWABLE TABLETS